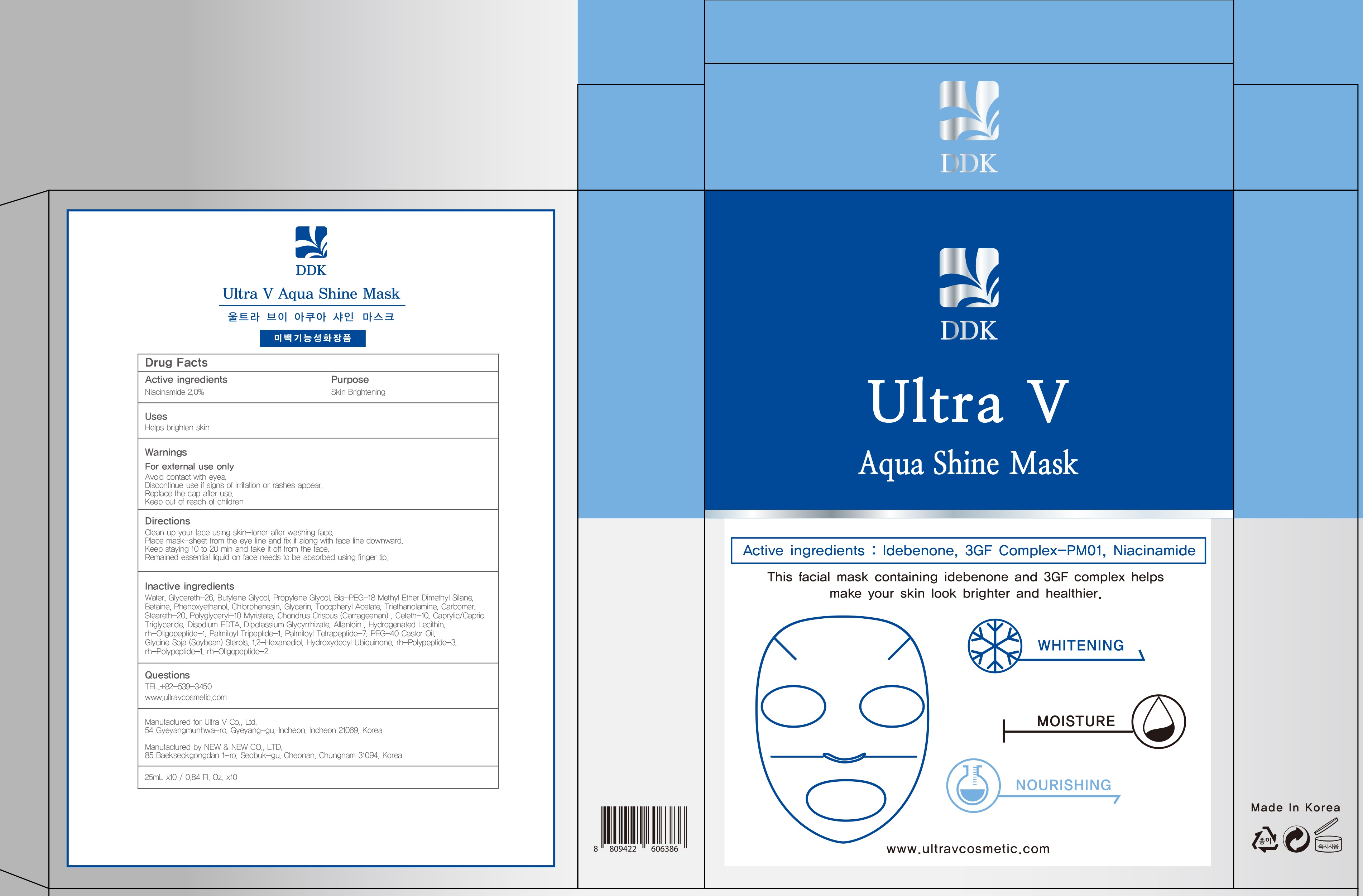 DRUG LABEL: Ultra V AQUA SHINE MASK
NDC: 71975-050 | Form: PATCH
Manufacturer: Ultra V Co., Ltd
Category: otc | Type: HUMAN OTC DRUG LABEL
Date: 20200401

ACTIVE INGREDIENTS: Niacinamide 0.5 g/25 mL
INACTIVE INGREDIENTS: Water; Glycereth-26

ACTIVE INGREDIENT

Active ingredients: Niacinamide 2.0%

INACTIVE INGREDIENT

Inactive ingredients: Water, Glycereth-26 , Butylene Glycol , Propylene Glycol, Bis-PEG-18 Methyl Ether Dimethyl Silane , Betaine , Phenoxyethanol, Chlorphenesin, Glycerin , Tocopheryl Acetate , Triethanolamine , Carbomer , Steareth-20 , Polyglyceryl-10 Myristate , Chondrus Crispus (Carrageenan) , Ceteth-10 , Caprylic/Capric Triglyceride , Disodium EDTA, Dipotassium Glycyrrhizate, Allantoin , Hydrogenated Lecithin , rh-Oligopeptide-1, Palmitoyl Tripeptide-1, Palmitoyl Tetrapeptide-7, PEG-40 Castor Oil , Glycine Soja (Soybean) Sterols , 1,2-Hexanediol , Hydroxydecyl Ubiquinone , rh-Polypeptide-3 , rh-Polypeptide-1 , rh-Oligopeptide-2

PURPOSE

Purpose: Skin Brightening

WARNINGS

Warnings: For external use only. Avoid contact with eyes. Discontinue use if signs of irritation or rashes appear. Replace the cap after use. Keep out of reach of children.

KEEP OUT OF REACH OF CHILDREN

Uses

Helps brighten skin

Directions

Directions: Clean up your face using skin-toner after washing face. Place mask-sheet from the eye line and fix it along with face line downward. Keep staying 10 to 20 min and take it off from the face. Remained essential liquid on face needs to be absorbed using finger tip.

QUESTIONS

TEL,+82-539-3450

www.ultravcosmetic.com